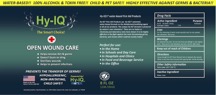 DRUG LABEL: HY-IQ OPEN WOUND CARE
NDC: 76701-363 | Form: SPRAY
Manufacturer: HAND SANITIZER LLC
Category: otc | Type: HUMAN OTC DRUG LABEL
Date: 20210629

ACTIVE INGREDIENTS: HYDROGEN CATION 10 mg/1 mL
INACTIVE INGREDIENTS: WATER 940 mg/1 mL; UREA 50 mg/1 mL

ACTIVE INGREDIENT

Hy- IQ Water ([H9O4] | [H5O2])

Hydrogen Cation .77%

PURPOSE

ANTISEPTIC

USES

FOR THE CLEANING OF MINOR ACUTE WOUNDS SUCH AS CUTS, GRAZES, SKIN ABRASIONS AND SORES.

WARNINGS

FOR EXTERNAL USE ONLY. DO NOT USE IF YOU ARE ALLERGIC TO ANY INGREDIENTS. STOP USE IF A RASH DEVELOPS AND ASK A DOCTOR RIGHT AWAY.

KEEP OUT OF REACH OF CHILDREN

DIRECTIONS

SPRAY ENOUGH Hy-IQ® OPEN WOUND CARE TO DAMPEN THE WOUND. ALLOW TO DRY, THEN DRESS WOUND WITH APPROPRIATE, STERILE DRESSING.

OTHER SAFETY INFORMATION

STORE UNDER 110 F (43 C)

INACTIVE INGREDIENT SECTION

WATER UREA